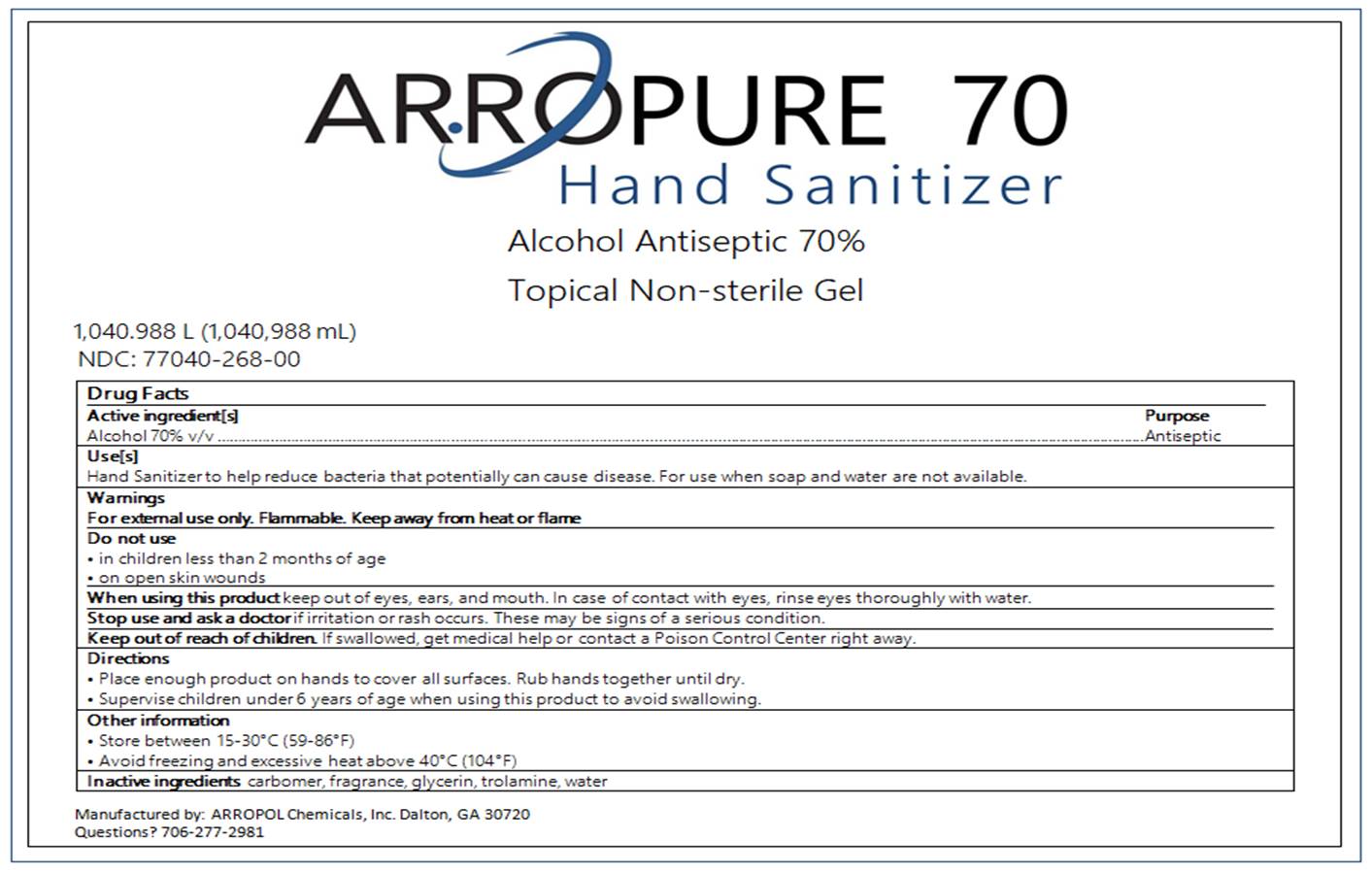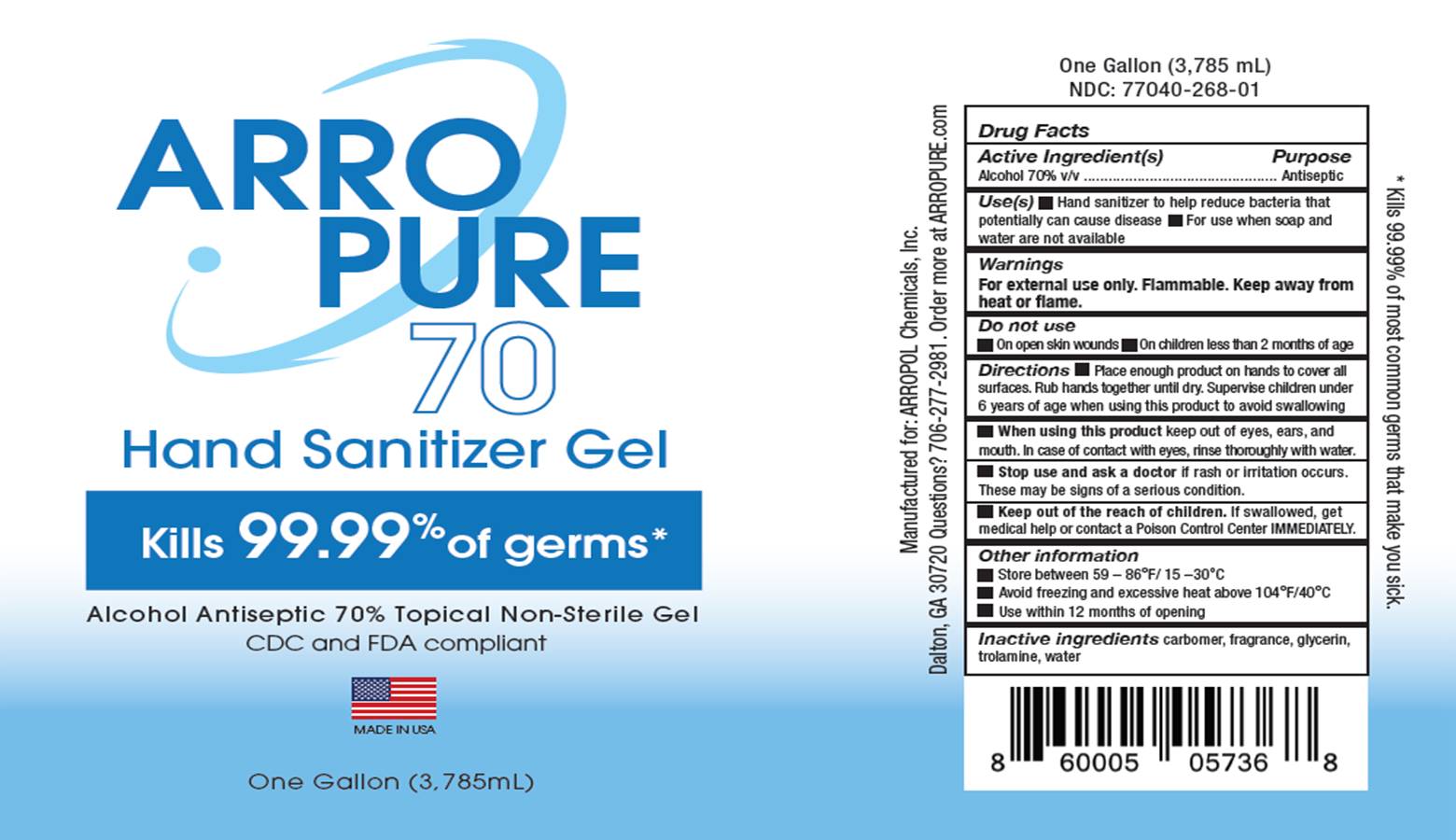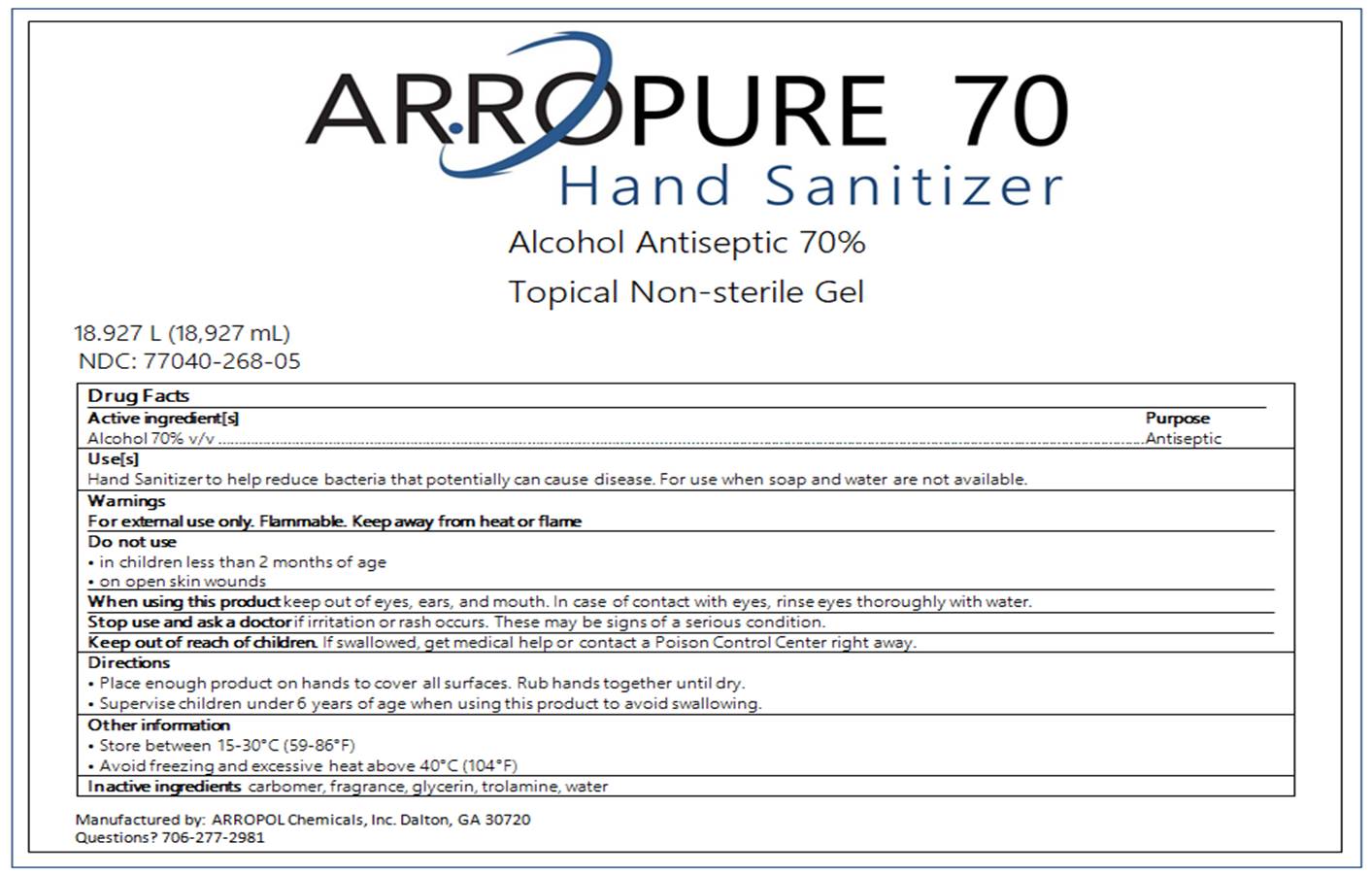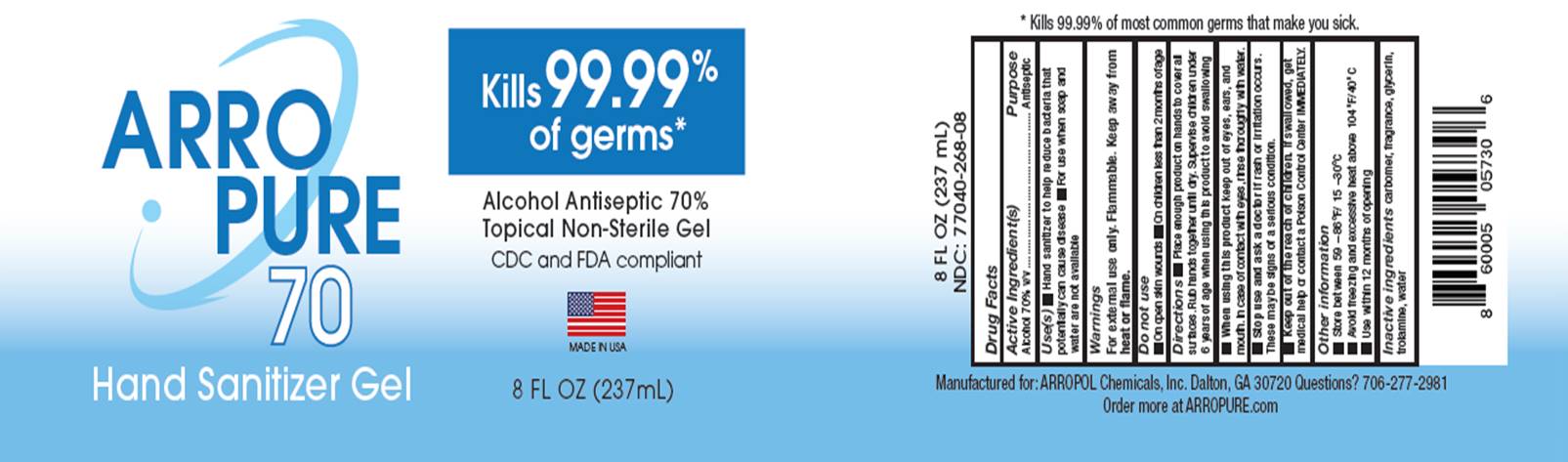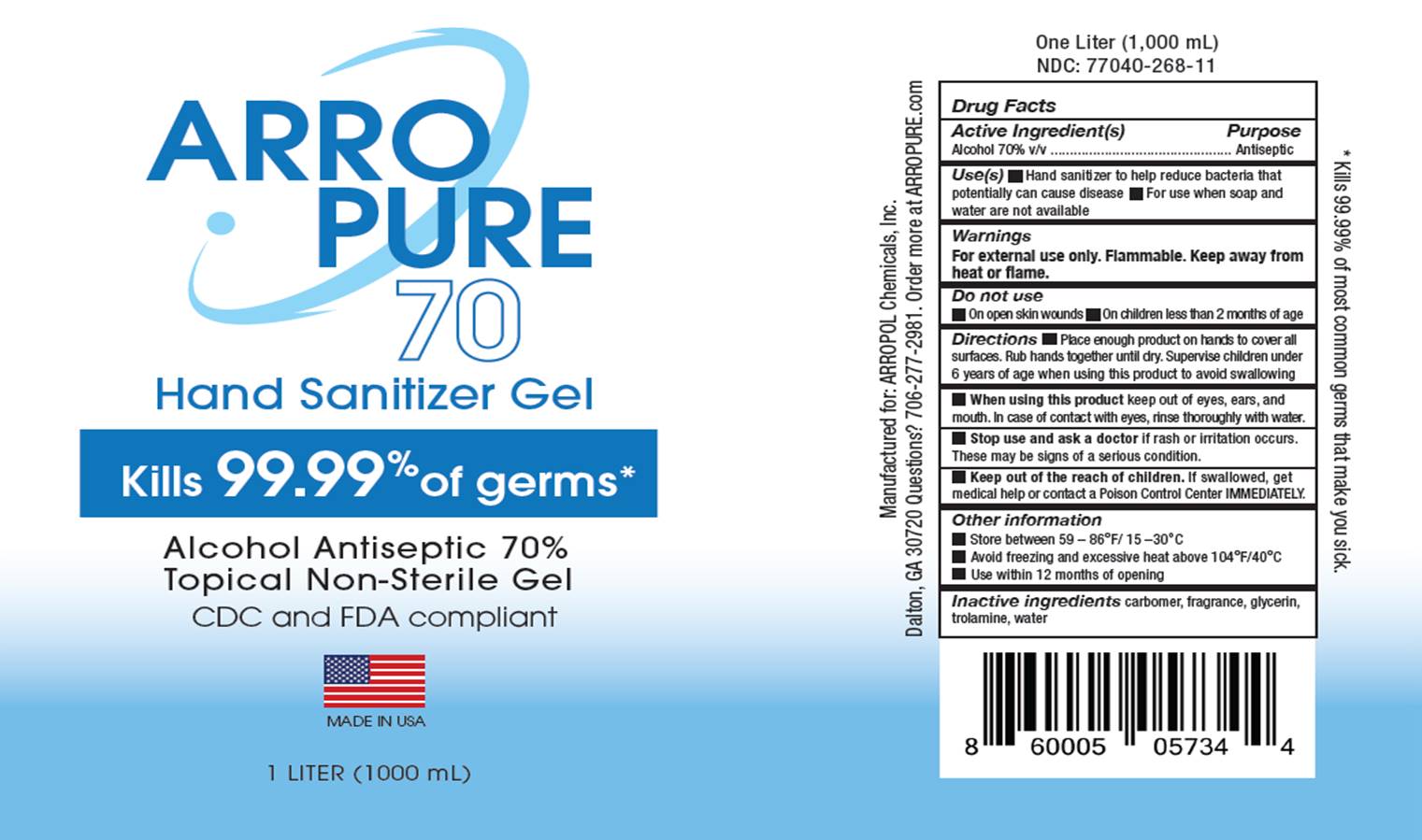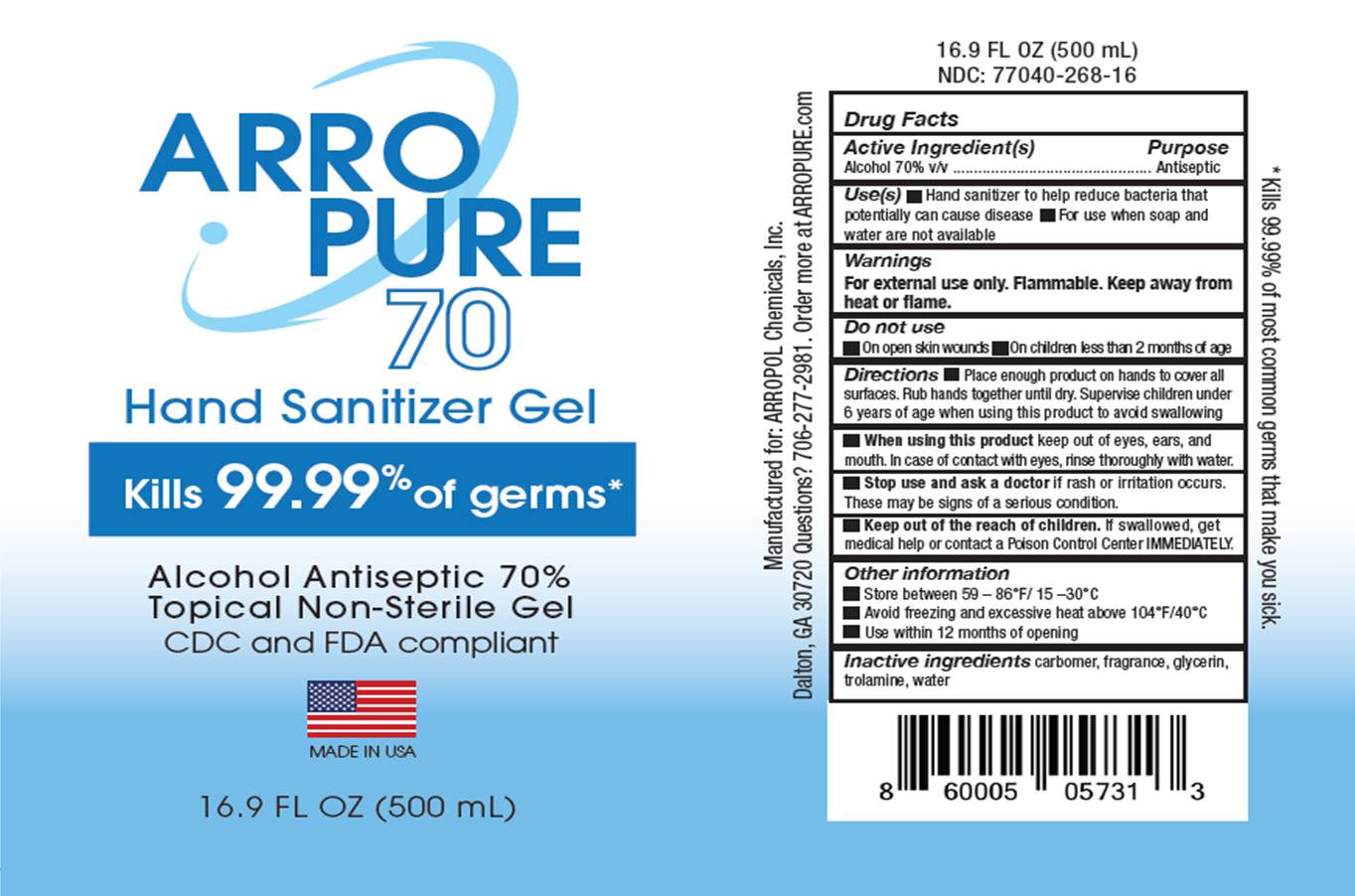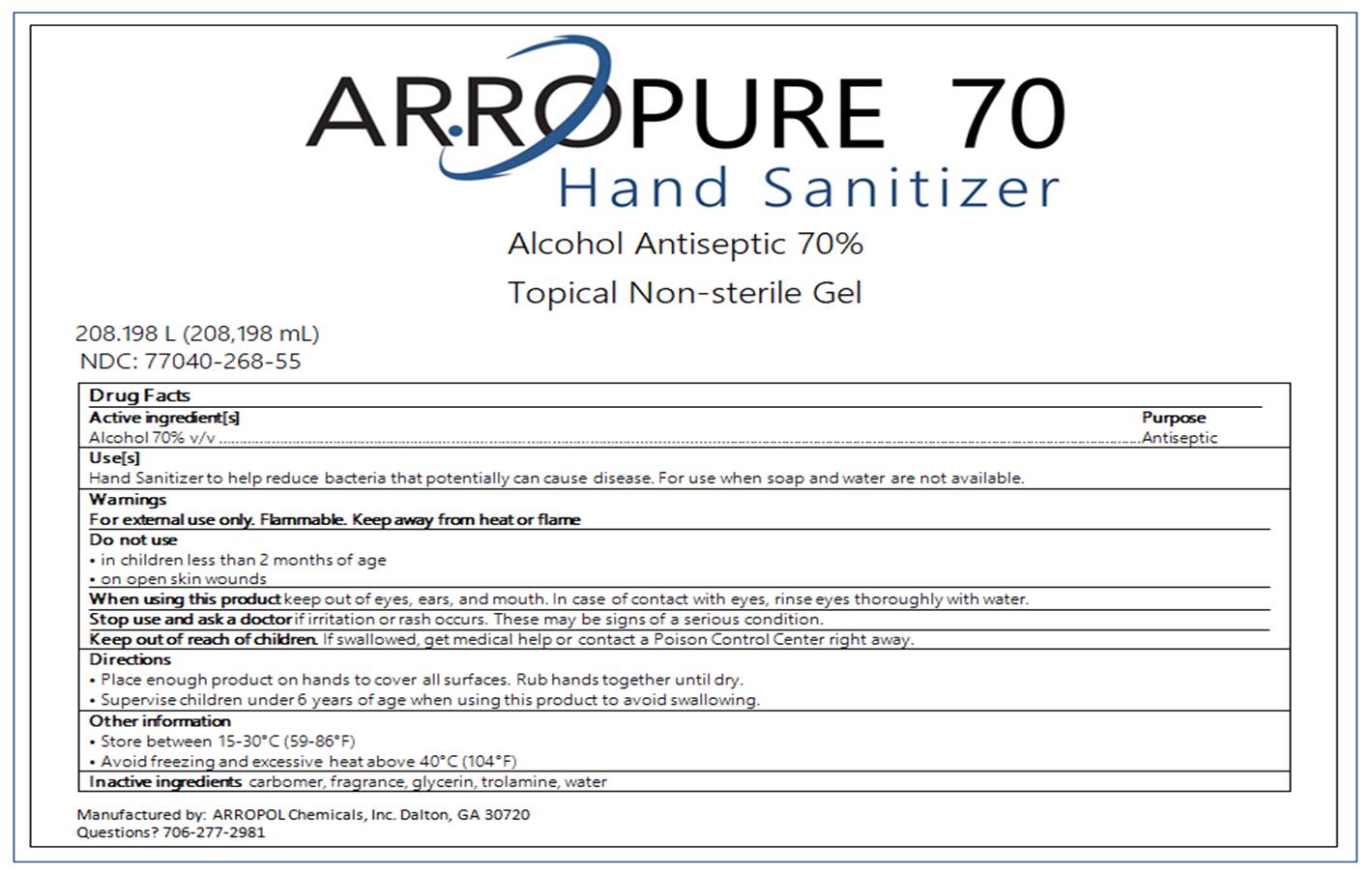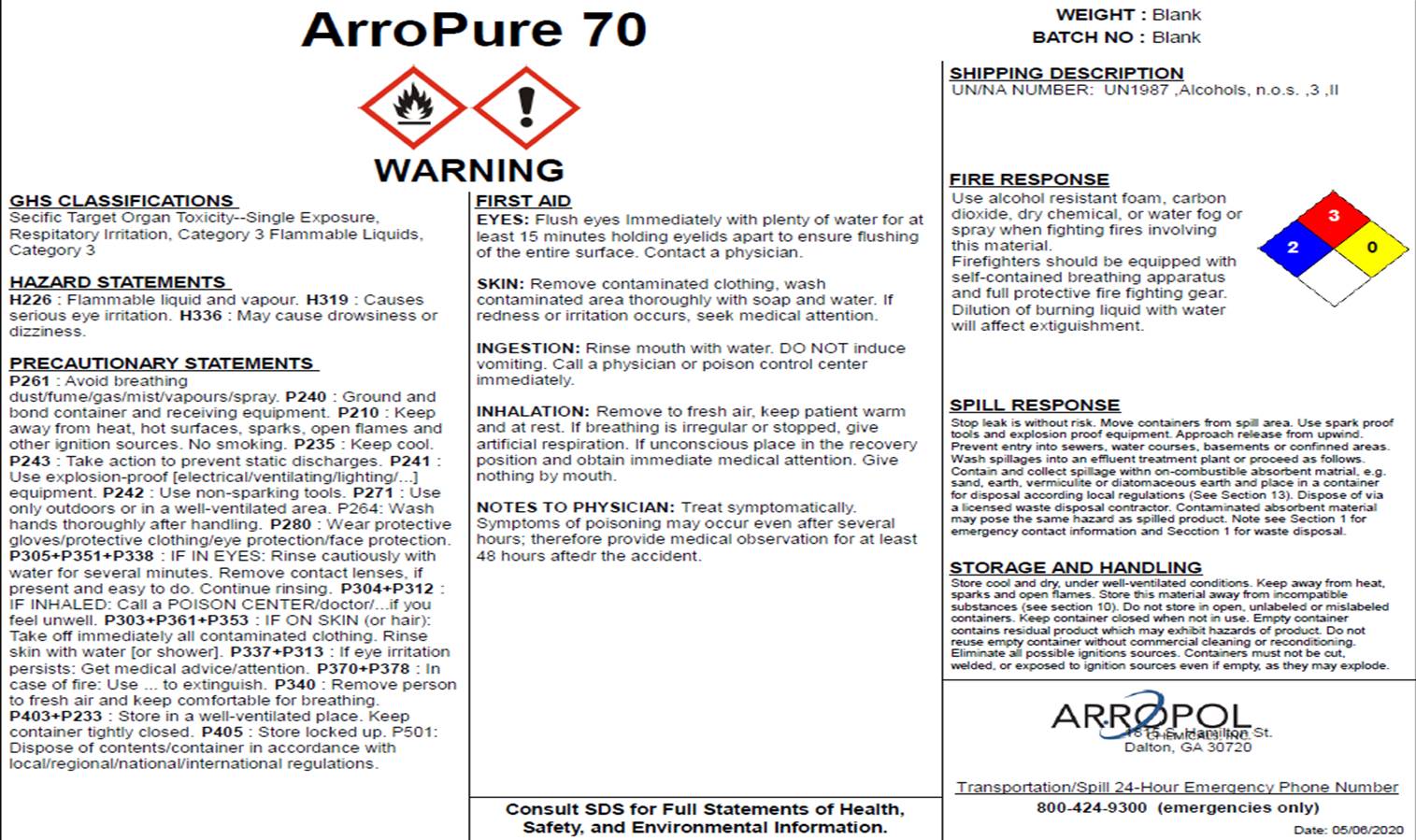 DRUG LABEL: ArroPure 70
NDC: 77040-268 | Form: GEL
Manufacturer: ARROPOL Chemicals, Inc.
Category: otc | Type: HUMAN OTC DRUG LABEL
Date: 20220113

ACTIVE INGREDIENTS: ALCOHOL 70 mL/100 mL
INACTIVE INGREDIENTS: WATER; CARBOMER HOMOPOLYMER, UNSPECIFIED TYPE; TROLAMINE; GLYCERIN 1 mL/100 mL

ArroPure 70
Alcohol Antiseptic 70%

Active Ingredient[s]

Alcohol 70% v/v. Purpose: Antiseptic

Purpose

Antiseptic, Hand Sanitizer

Use

Hand Sanitizer to help reduce bacteria that potentially can cause disease.

For use when soap and water are not available.

Warnings

For external use only. Flammable. Keep away from heat or flame.

Do not use

- in children less than 2 months of age
- on open skin wounds

When using this product keep out of eyes, ears, and mouth. In case of contact with eyes, rinse eyes thoroughly with water.

Stop use and ask a doctor if irritation or rash occurs. These may be signs of a serious condition.

Keep out of reach of children. If swallowed, get medical help or contact a Poison Control Center right away.

Stop use and ask a doctor if irritation or rash occurs. These may be signs of a serious condition.

Keep out of reach of children. If swallowed, get medical help or contact a Poison Control Center right away.

Directions

- Place enough product on hands to cover all surfaces. Rub hands together until dry.
- Supervise children under 6 years of age when using this product to avoid swallowing.

Other Information

- Store between 15-30°C (59-86°F)
- Avoid freezing and excessive heat above 40°C (104°F)

Inactive ingredients

carbomer, fragrance, glycerin, trolamine, water

Package Label

Label for all packages

18,927 mL NDC: 77040-268-05

208,198 mL NDC: 77040-268-55

1,040,988 mL NDC: 77040-268-00

3,785 mL NDC: 77040-268-01

1,000 mL NDC: 77040-268-11

500 mL NDC: 77040-268-16

237 mL NDC: 77040-268-08